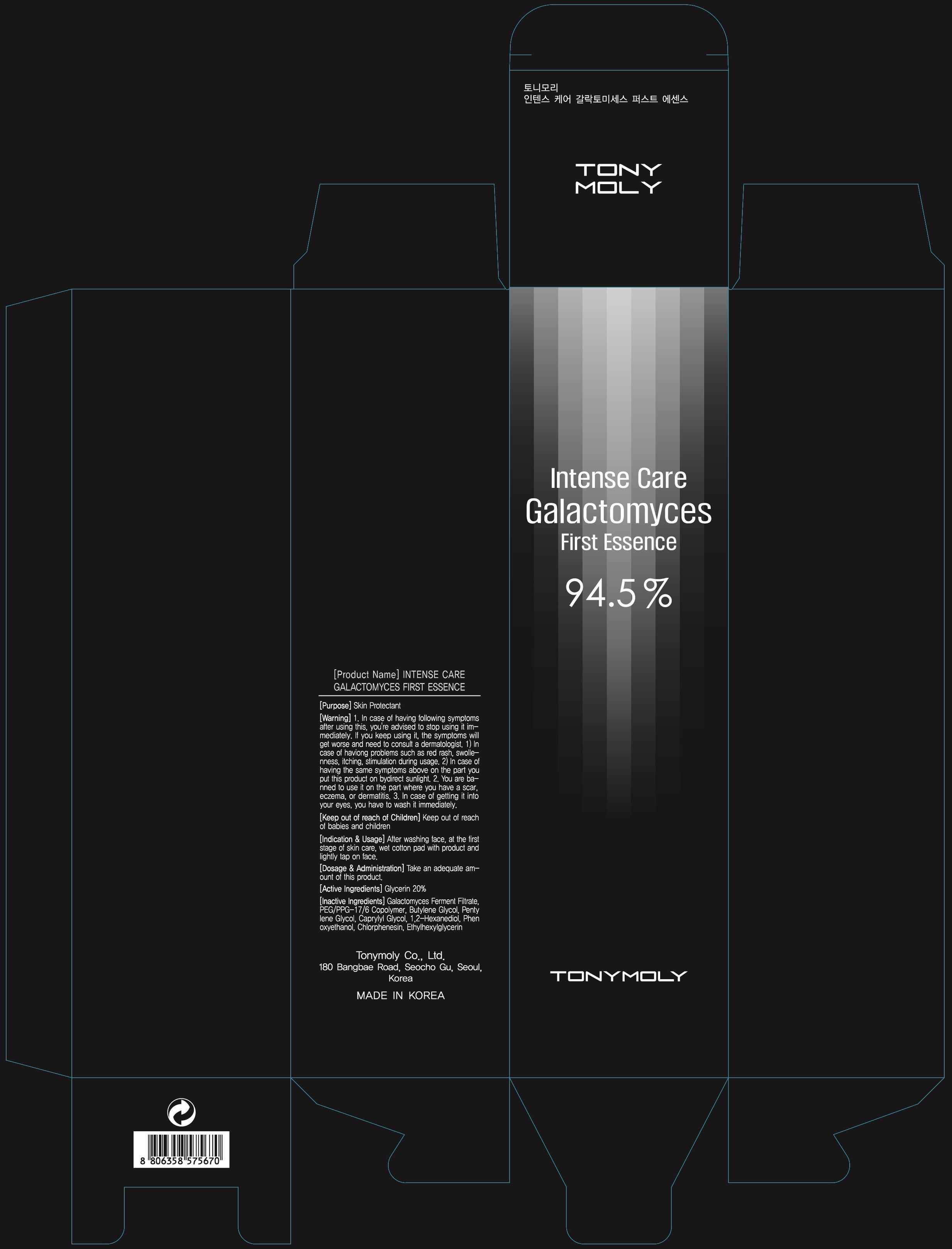 DRUG LABEL: INTENSE CARE GALACTOMYCES FIRST ESSENCE
NDC: 59078-003 | Form: CREAM
Manufacturer: TONYMOLY CO., LTD.
Category: otc | Type: HUMAN OTC DRUG LABEL
Date: 20130713

ACTIVE INGREDIENTS: Glycerin 31 mg/155 mL
INACTIVE INGREDIENTS: Butylene Glycol; Pentylene Glycol

ACTIVE INGREDIENT

Active Ingredient: Glycerin 20%

INACTIVE INGREDIENT

Inactive Ingredients:
Galactomyces Ferment Filtrate, PEG/PPG-17/6 Copolymer, Butylene Glycol, Pentylene Glycol, Caprylyl Glycol, 1,2-Hexanediol, Phenoxyethanol, Chlorphenesin, Ethylhexylglycerin

PURPOSE

PURPOSE: Skin Protectant

WARNINGS

1. In case of having following symptoms after using this, you're advised to stop using it immediately. If you keep using it, the symptoms will get worse and need to consult a dermatologist.
1) In case of haviong problems such as red rash, swollenness, itching, stimulation during usage.
2) In case of having the same symptoms above on the part you put this product on by direct sunlight.
2. You are banned to use it on the part where you have a scar, eczema, or dermatitis.
3. In case of getting it into your eyes, you have to wash it immediately.

KEEP OUT OF REACH OF CHILDREN

Keep out of reach of babies and children

INDICATIONS AND USAGE: After washing face, at the first stage of skin care, wet cotton pad with product and lightly tap on face.

DOSAGE AND ADMINISTRATION: Take an adequate amount of this product.